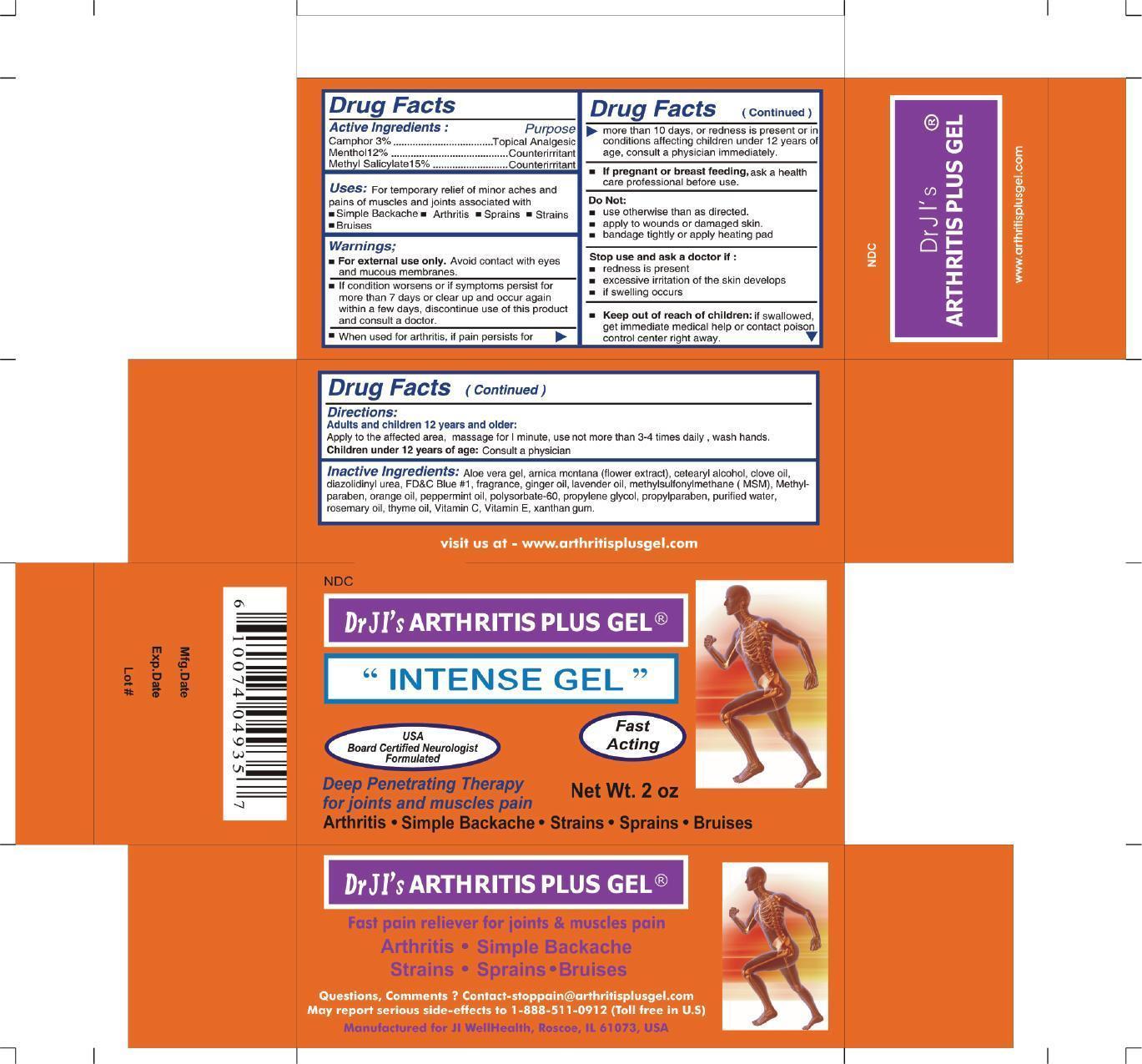 DRUG LABEL: Arthritis Plus Gel
                
NDC: 50810-2000 | Form: CREAM
Manufacturer: JI Well Health Company
Category: otc | Type: HUMAN OTC DRUG LABEL
Date: 20130605

ACTIVE INGREDIENTS: CAMPHOR (NATURAL) 3 mg/100 mg; MENTHOL 12 mg/100 mg; METHYL SALICYLATE 15 mg/100 mg
INACTIVE INGREDIENTS: ALOE VERA LEAF; ARNICA MONTANA; CETOSTEARYL ALCOHOL; CLOVE OIL; DIAZOLIDINYL UREA; FD&C BLUE NO. 1; GINGER OIL; LAVENDER OIL; DIMETHYL SULFONE; METHYLPARABEN; ORANGE OIL; PEPPERMINT OIL; POLYSORBATE 60; PROPYLENE GLYCOL; PROPYLPARABEN; WATER; ROSEMARY OIL; THYME OIL; ASCORBIC ACID; .ALPHA.-TOCOPHEROL; XANTHAN GUM

Drug Facts

Inactive Ingredients

Aloe vera gel, amica montana (flower extract), cetaryl alcohol, clove oil,
diazolidimyl urea, FD C Blue #1, frangrance, ginger oil, lavender oil,
methylsulfonylmethane (MSM), Methyl paraben, orange oil.
peppermint oil, polysorbate 60, propylene glycol, propylparaben,
purified water, rosemary oil, thyme oil, Vitamin C,
Vitamin E, xanthan gum

Active Ingredients

Camphor 3%

Methol 12%

Methyl Salicylate 15%

Purpose

Topical Analgesic

Counterirritant

Counterirritant

Uses

For temporary relief of minor aches and pains of muscles and joints associated with:

-Simple Backache

-Arthritis

-Sprains

-Strains

-Bruises

Warnings:

For external use only. Avoid contact with

eyes and mucous membranes

-If condition worsens or if symptoms persist for more than 7 days

or clear up and appear again within a few days, discontinue use of this

product and consult a doctor.

-When used for arthritis, if pain persists for more than 10 days or redness

is present or in conditions affecting children under 12 years of age, consult

a physician immediately.

PREGNANCY OR BREAST FEEDING

If pregnant or breast feeding, ask a health care professional before use.

Keep out of reach of children: If swallowed, get immediate

medical help or contact poison control center right away

Directions:

Adults and children 12 years of age and older:

apply to the affected area, massage for 1 minute,

use not more than 3-4 times daily, wash hands.

Children under 12 years of age: Consult a physician